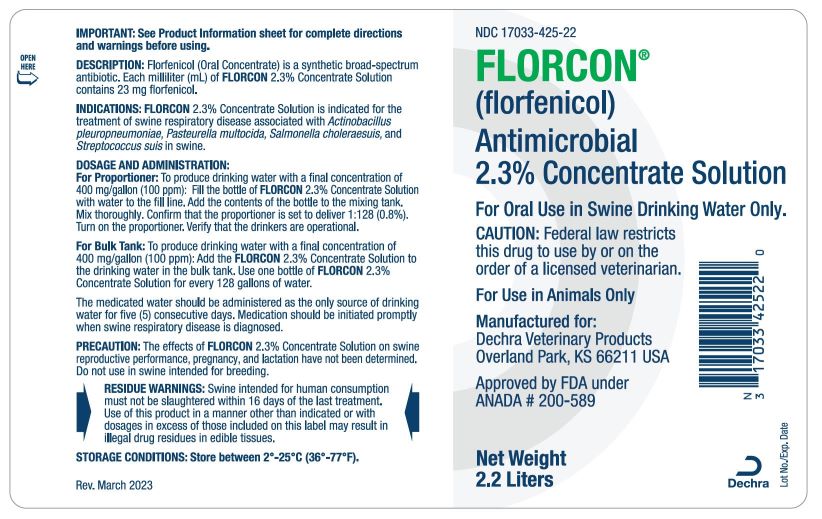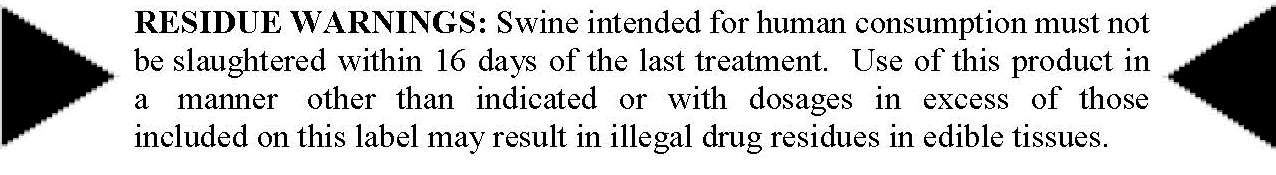 DRUG LABEL: FLORCON
NDC: 17033-425 | Form: SOLUTION, CONCENTRATE
Manufacturer: Dechra Veterinary Products
Category: animal | Type: PRESCRIPTION ANIMAL DRUG LABEL
Date: 20230509

ACTIVE INGREDIENTS: FLORFENICOL 23 mg/1 mL

FLORCON 2.3% Concentrate Solution

FLORCON

(florfenicol)

An Antimicrobial 2.3% Concentrate Solution

For Oral Use in Swine Drinking Water Only.

CAUTION: Federal law restricts this drug to use by or on the order of a licensed veterinarian.

Approved by FDA under ANADA #200-589

For use in Animals Only

IMPORTANT: See Product Information sheet for complete directions and warnings before using.

DESCRIPTION

DESCRIPTION: FLORCON (florfenicol) Oral Concentrate is a synthetic broad-spectrum antibiotic. Each milliliter (mL) of FLORCON 2.3% Concentrate Solution contains 23 mg florfenicol.

INDICATIONS AND USAGE

INDICATIONS: FLORCON 2.3% Concentrate Solution is indicated for the treatment of swine respiratory disease associated with Actinobacillus pleuropneumoniae, Pasteurella multocida, Salmonella choleraesuis, and Streptococcus suis in swine.

DOSAGE AND ADMINISTRATION:

For Proportioner: To produce drinking water with a final concentration of 400 mg/gallon (100 ppm): Fill the bottle of FLORCON 2.3% Concentrate Solution with water to the fill line. Add the contents of the bottle to the mixing tank. Mix thoroughly. Confirm that the proportioner is set to deliver 1:128 (0.8%). Turn on the proportioner. Verify that the drinkers are operational.

For Bulk Tank: To produce drinking water with a final concentration o f 400 mg/gallon (100 ppm): Add the FLORCON 2.3% Concentrate Solution to the drinking water in the bulk tank. Use one bottle of FLORCON 2.3% Concentrate Solution for every 128 gallons of water.

The medicated water should be administered as the only source of drinking water for five (5) consecutive days. Medication should be initiated promptly when swine respiratory disease is diagnosed.

PRECAUTIONS

PRECAUTIONS: Do not use this product at any other proportioner setting. This will result in precipitation of product. This product is not recommended for use in automatic water proportioners if water hardness is greater than 275 ppm. Water proportioners should be tested for accuracy before use. Do not use or store this product in galvanized metal watering systems or containers. Do not operate chlorinators while administering medication.

WARNINGS

WARNINGS: This product contains material that can be irritating to skin and eyes. Avoid direct contact with skin, eyes, and clothes. In case of accidental eye exposure, flush with water for 15 minutes. In case of accidental skin exposure, wash with soap and water. Remove contaminated clothing. Consult a physician if irritation persists. The Safety Data Sheet (SDS) contains more detailed occupational safety information.

NOT FOR HUMAN USE. KEEP OUT OF REACH OF CHILDREN.

CONTACT INFORMATION: To report suspected adverse drug events, for technical assistance or to obtain a copy of the Safety Data Sheet (SDS), contact Dechra Veterinary Products at 1-866-933-2472. For additional information about adverse drug experience reporting for animal drugs, contact FDA at 1-888-FDA-VETS or online at http://www.fda.gov/reportanimalae

PRECAUTIONS

PRECAUTION: The effects of FLORCON 2.3% Concentrate Solution on swine reproductive performance, pregnancy, and lactation have not been determined. Do not use in swine intended for breeding.

ADVERSE REACTIONS

ADVERSE REACTION: Perianal inflammation may occur transiently following treatment.

CLINICAL PHARMACOLOGY

CLINICAL PHARMACOLOGY: Florfenicol is a bacteriostatic agent whose antimicrobial activity is linked to time above MIC.

The pharmacokinetic disposition of FLORCON 2.3% Concentrate Solution was evaluated in swine following oral gavage dosing (15 mg/kg), intravenous (IV) dosing (15 mg/kg), and during a five (5) day course of ad libitum administration in drinking water (100 ppm) (Table 1). Despite the rapid elimination seen after IV injection or oral gavage dosing, when administered in medicated drinking water, florfenicol concentrations in the serum of most swine were maintained well above 1.0 mcg/mL for the majority of the (5) day dosing interval. These results are consistent with product effectiveness when administered in drinking water concentrations of 100 ppm over a five (5) day dosing period.

Although the extent of oral drug absorption (F) tended to be variable (24% to 97% following a single oral gavage dose), florfenicol was rapidly absorbed. Its terminal elimination half-life (T1/2) was also rapid, ranging between two (2) to three (3) hours.

The average systemic clearance (CLB) following IV administration was 5.6 mL/kg/min. Since the florfenicol steady state volume of distribution (VDSS) closely approximates that of total body water, peripheral tissue concentrations are expected to be similar to those concentrations observed in serum.

Table 1. Pharmacokinetic Parameter Values of Florfenicol
following IV or Gavage Dosing
Parameter | Mean Value (% CV)
Vdssa (L/kg) | 0.95 (6)
CLBa (mL/kg/min) | 5.57 (11)
T ½a (hrs) | 2.2 (14)
Fb (%) | 24-97
aparameter estimate based on intravenous data
bparameter range based upon a single oral gavage dose

MICROBIOLOGY

MICROBIOLOGY: Florfenicol is a synthetic broad-spectrum antibiotic active against many gram-negative and gram-positive bacteria isolated from domestic animals. It acts by inhibiting bacterial protein synthesis. In vivo and in vitro activity has been demonstrated against commonly isolated pathogens involved in swine respiratory disease including Actinobacillus pleuropneumoniae, Pasteurella multocida, Salmonella choleraesuis, and Streptococcus suis.

The minimum inhibitory concentration (MIC) of florfenicol was determined for isolates obtained from natural respiratory infections of swine from 1990-2001 (Table 2). Susceptibility testing followed the methods of the National Committee of Clinical Laboratory Standards. Reference strains included Escherichia coli ATCC 25922 with a QC range of 2-8 mcg/mL and Actinobacillus pleuropneumoniae ATCC 27090 with a QC range of 0.25-1 mcg/mL.

Table 2. MIC Values of Florfenicol Against
Bacterial Isolates from Swine
Organism | Isolate; Numbers | MIC90 *; (mcg/mL) | MIC Range; (mcg/mL)
Actinobacillus; pleuropneumoniae | 360 | 0.50 | ≤0.125-2.0
Pasteurella multocida | 335 | 0.50 | ≤0.125-2.0
Salmonella; choleraesuis | 46 | 4.0 | 2.0-4.0
Streptococcus suis | 203 | 2.0 | 0.5-2.0

*The minimum inhibitory concentration for 90 % of the isolates

ANIMAL PHARMACOLOGY AND OR TOXICOLOGY

ANIMAL SAFETY: A target animal safety study was conducted to evaluate the tolerance and effects of florfenicol when orally administered to swine via the drinking water at a rate of 400, 1200, and 2000 mg/gal (1x, 3x, or 5x the clinical dose) for fifteen (15) to sixteen (16) consecutive days (3x the clinical duration), and at 4000 mg/gal (10x clinical dose) for five (5) to six (6) consecutive days (1x the clinical duration).

Transient treatment-related constipation and anal swelling were seen in the 3x, 5x, and 10x treatment groups. The constipation in these groups was attributed in part to decreased water consumption during the medication period. There was a decrease in weight gains for the 3x, 5x, and 10x treatment groups compared with the nonmedicated control group. Transient treatment-related decreases in feed consumption were seen in the 3x, 5x, and 10x treatment groups compared with the nonmedicated control group. Transient treatment-related decreases in water consumption were noted in all test article-treated groups (1x, 3x, 5x, and 10x) compared with the nonmedicated control group.

The results show that FLORCON 2.3% Concentrate Solution can be safely administered to swine according to the recommended clinical regimen of 400 mg/gal in the drinking water for five (5) consecutive days.

STORAGE AND HANDLING

STORAGE CONDITIONS: Store between 2°-25°C (36°-77°F).

HOW SUPPLIED

HOW SUPPLIED: FLORCON 2.3% Concentrate Solution is supplied in one gallon plastic bottles with 2.2 liter fill.

Manufactured for:
Dechra Veterinary Products
Overland Park, KS 66211

Rev. May 2023